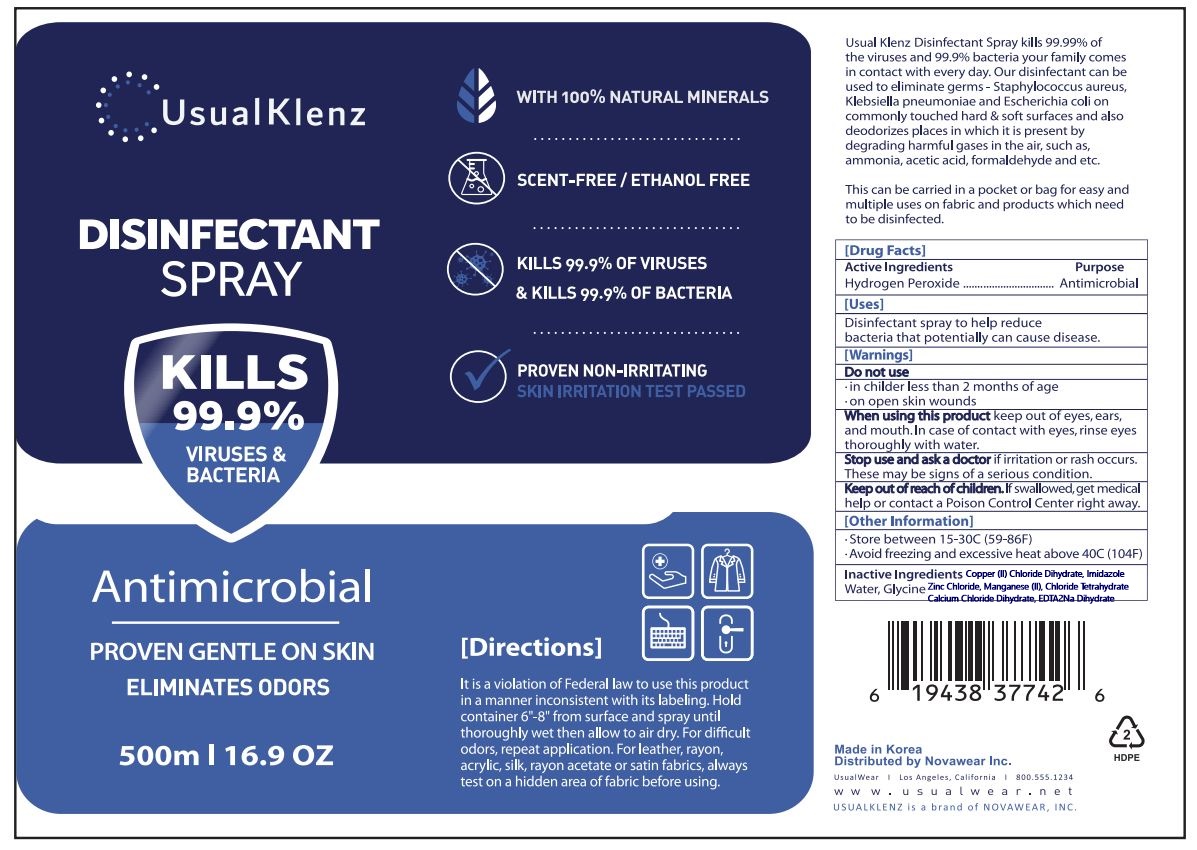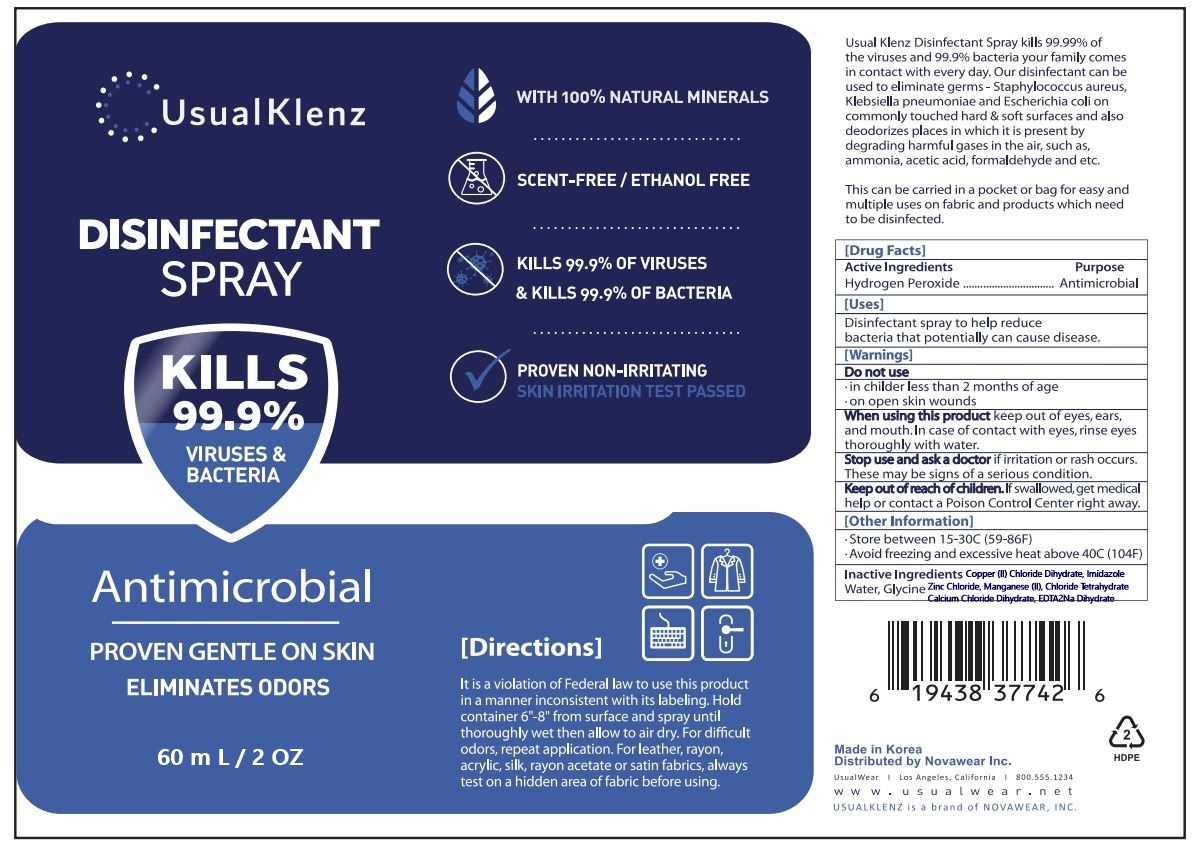 DRUG LABEL: USUALKLENZ DISINFECTANTSPRAY
NDC: 81057-302 | Form: LIQUID
Manufacturer: NOVAWEAR INC.
Category: otc | Type: HUMAN OTC DRUG LABEL
Date: 20211206

ACTIVE INGREDIENTS: HYDROGEN PEROXIDE 5 mg/100 mL
INACTIVE INGREDIENTS: CALCIUM CHLORIDE; IMIDAZOLE; ZINC CHLORIDE; MANGANESE CHLORIDE; EDETIC ACID DIHYDRATE; CUPRIC CHLORIDE; WATER; GLYCINE

Active Ingredients

Hydrogen Peroxide 5%

Purpose

Antimicrobial

Uses

Disinfectant spray to help reduce bacteria that potentially can cause diesease.

Warnings

For external use only

Warnings

in childer less than 2 months of age

on open skin wounds

Warnings

When using this product keep out of eyes, ears, and mouth, In case of contact with eyes, rinse eyes thoroughly with water.

Warnings

Stop use and ask a doctor if irritation or rash occurs.

These may be signs of a serious condition.

Warnings

Keep out of reach of children. If swallowed, get medical help or contact a Poison Control Center right away.

Other Information

Store between 15-30C (59-86F)

Avoid freezing and excessive heat above 40C (104F)

Directions

It is a violation of Federal law to use this product in a manner inconsistent with its labeling. Hold container 6"-8' from surface and spray until thoroughly wet then allow to air dry. For difficult odors, repeat application. For leather, rayon, acrylic, silk, rayon acetate or satin fabrics, always test on a hidden area of fabric before using.

Inactive Ingredients

Water, Glycine, Zinc Chloride, Manganese (II) Chloride Tetrahydrate, Calcium Chloride Dihydrate, Copper (II) Chloride Dihydrate, Imidazole, EDTA2Na Dihydrate